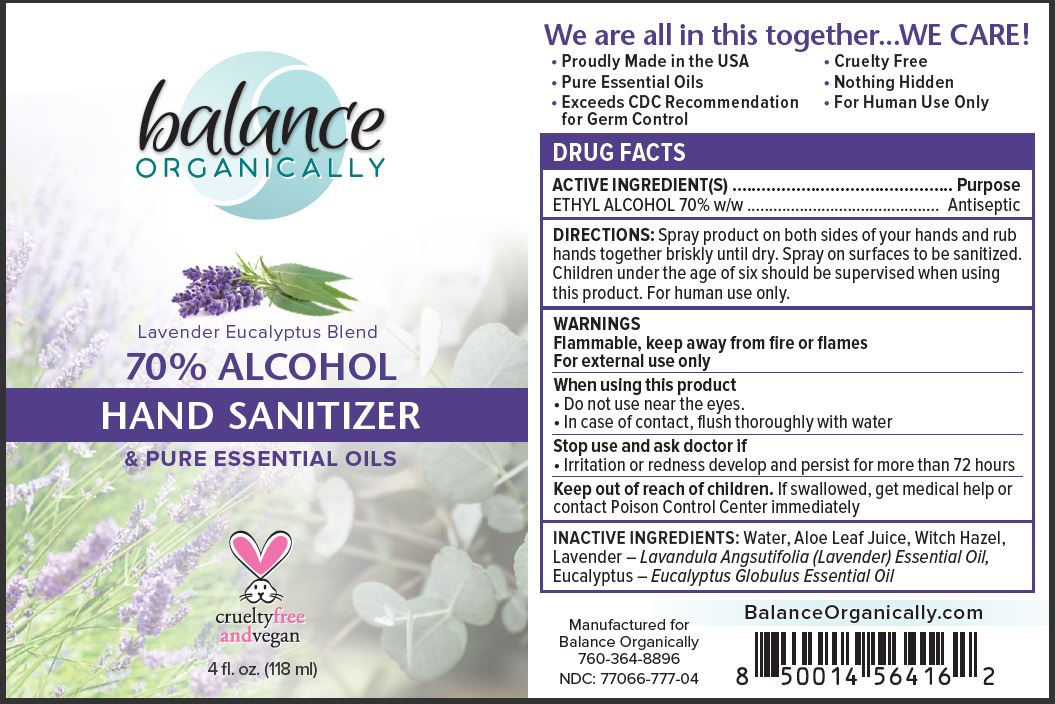 DRUG LABEL: HAND SANITIZER
NDC: 77066-777 | Form: SPRAY
Manufacturer: ENLIGHTENED LLC
Category: otc | Type: HUMAN OTC DRUG LABEL
Date: 20201102

ACTIVE INGREDIENTS: ALCOHOL 70 mL/100 mL
INACTIVE INGREDIENTS: WATER; ALOE VERA LEAF; WITCH HAZEL; LAVENDER OIL; EUCALYPTUS OIL

BALANCE ORGANICALLY - LAVENDER EUCALYPTUS BLEND - 70% ALCOHOL HAND SANITIZER AND PURE ESSENTIAL OILS

ACTIVE INGREDIENT

ETHYL ALCOHOL 70% W/W

PURPOSE

ANTISEPTIC

USES

TO DECREASE BACTERIA ON THE SKIN. RECOMMENDED FOR REPEATED USE.

WARNINGS

Flammable, keep away from fire or flames

For external use only

When using this product

- Do not use near the eyes.
- In case of contact, flush thoroughly with water

Stop use and ask doctor if

- Irritation or redness develop and persist for more than 72 hours

Keep out of reach of children. If swallowed, get medical help or contact Poison Control Center immediately

DIRECTIONS

Spray product on both sides of your hands and rub hands together briskly until dry. Spray on surfaces to be sanitized. Children under the age of six should be supervised when using this product. For human use only.

INACTIVE INGREDIENTS

Water, Aloe Leaf Juice, Witch Hazel, Lavender – Lavandula Angsutifolia (Lavender) Essential Oil, Eucalyptus – Eucalyptus Globulus Essential Oil